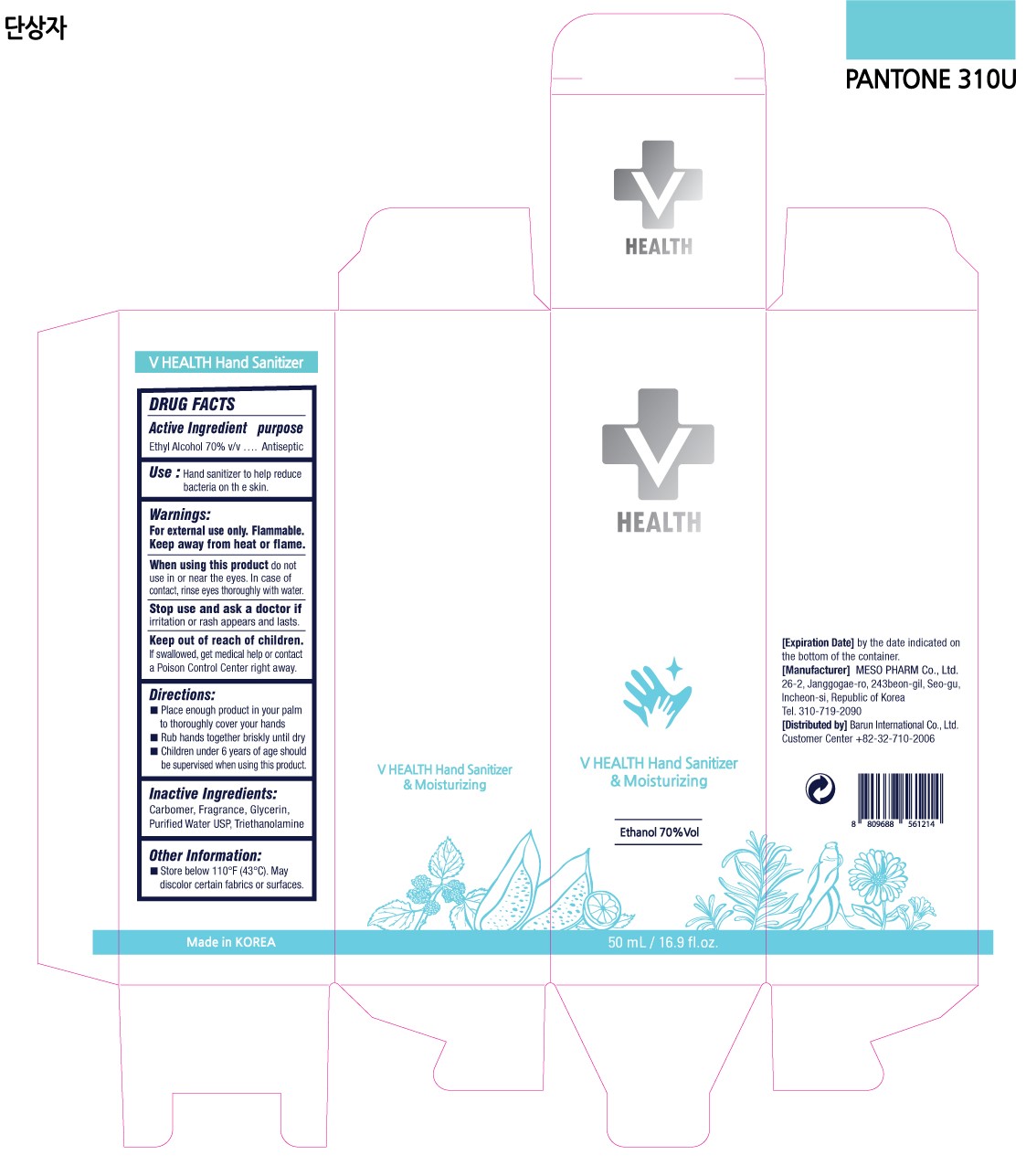 DRUG LABEL: V HEALTH Hand Sanitizer
NDC: 80604-100 | Form: GEL
Manufacturer: Barun International Inc.
Category: otc | Type: HUMAN OTC DRUG LABEL
Date: 20200917

ACTIVE INGREDIENTS: ALCOHOL 70 mL/100 mL
INACTIVE INGREDIENTS: CARBOMER HOMOPOLYMER TYPE B (ALLYL PENTAERYTHRITOL CROSSLINKED); GLYCERIN; TROLAMINE; WATER

This is a hand sanitizer manufactured according to the Temporary Policy for Preparation of Certain Alcohol-Based Hand Sanitizer Products During the Public Health Emergency (CoViD-19); Guidance for Industry.

The hand sanitizer is manufactured using only the following United States Pharmacopoeia (USP) grade ingredients in the preparation of the product (percentage in final product formulation) consistent with World Health Organization (WHO) recommendations:

1. Alcohol (ethanol) (USP or Food Chemical Codex (FCC) grade) (80%, volume/volume (v/v)) in an aqueous solution denatured according to Alcohol and Tobacco Tax and Trade Bureau regulations in 27 CFR part 20.
2. Glycerol (1.45% v/v).
3. Hydrogen peroxide (0.125% v/v).
4. Sterile distilled water or boiled cold water.

The firm does not add other active or inactive ingredients. Different or additional ingredients may impact the quality and potency of the product.

Active Ingredient(s)

Ethly Alcohol 70% v/v

Purpose

Antiseptic

Use

Hand sanitizer to help reduce bacteria on the skin.

Warnings

For external use only. Flammable. Keep away from heat or flame.

When using this product do not use in or near the eyes. In case of contact, rinse eyes thoroughly with water.

Stop use and ask a doctor if irritation or rash appears and lasts.

Keep out of reach of children. If swallowed, get medical help or contact a Poison Control Center right away.

Directions

- Place enough product in your palm to thoroughly cover your hands
- Rub hands together briskly until dry
- Children under 6 years of age should be supervised when using this product.

Inactive ingredients

Carbomer, Fragrance, Glycerin, Purified water USP, Triethanolamine

Other information

- Store below 110°F (43°C). May discolor certain fabrics or surfaces.